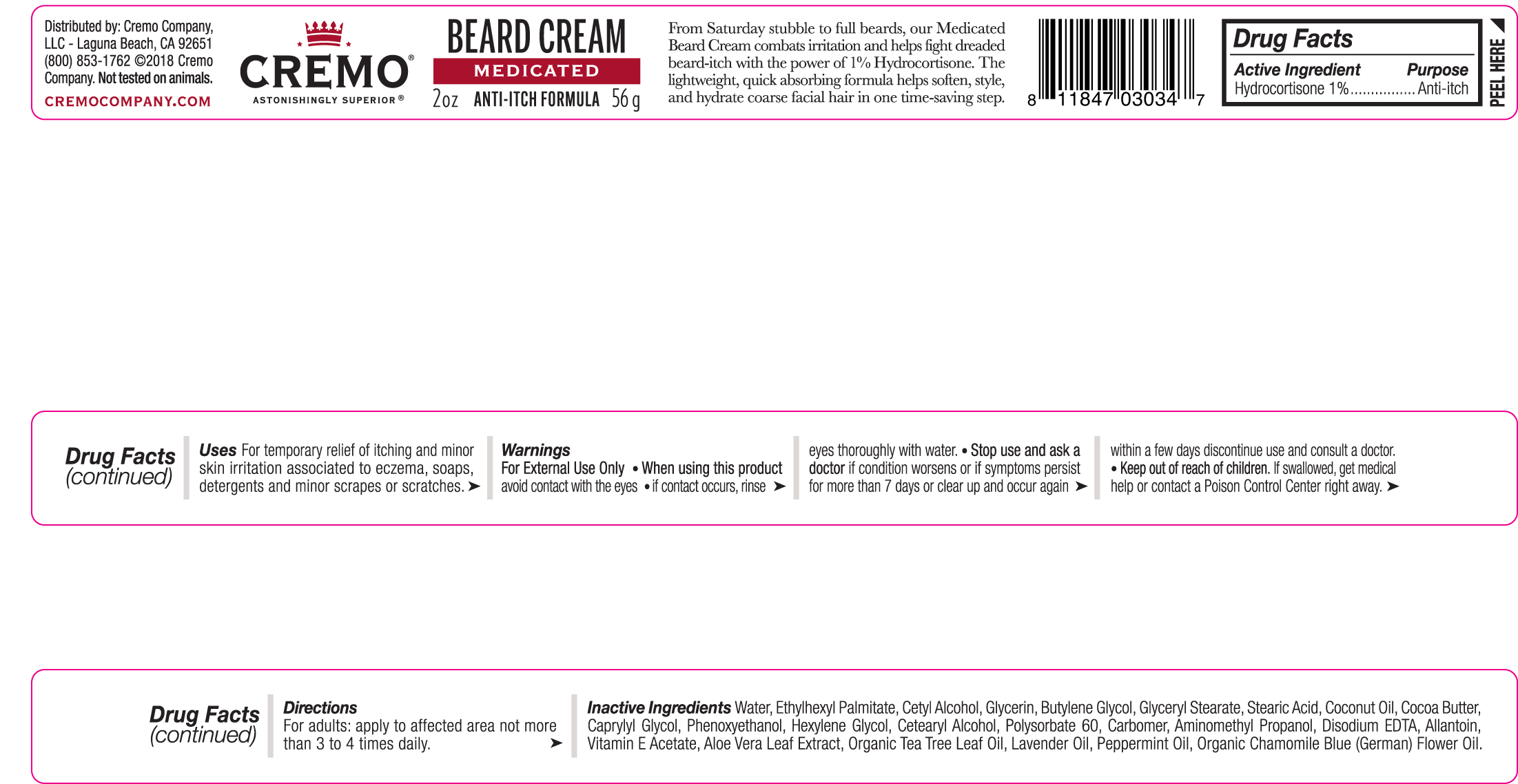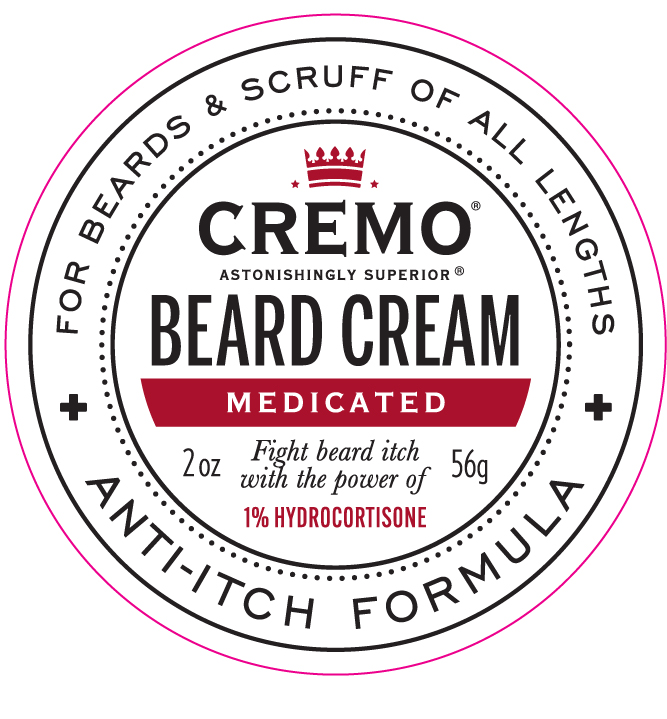 DRUG LABEL: Beard Medicated Cremo
NDC: 71825-107 | Form: CREAM
Manufacturer: Cremo company
Category: otc | Type: HUMAN OTC DRUG LABEL
Date: 20190117

ACTIVE INGREDIENTS: HYDROCORTISONE 1 g/100 g
INACTIVE INGREDIENTS: CETYL ALCOHOL; GLYCERIN; HEXYLENE GLYCOL; ALOE VERA LEAF; TEA TREE OIL; PEPPERMINT OIL; EDETATE DISODIUM ANHYDROUS; COCOA BUTTER; CETOSTEARYL ALCOHOL; CAPRYLYL GLYCOL; PHENOXYETHANOL; WATER; ETHYLHEXYL PALMITATE; COCONUT OIL; POLYSORBATE 60; CARBOXYPOLYMETHYLENE; AMINOMETHYLPROPANOL; ALLANTOIN; LAVENDER OIL; GLYCERYL MONOSTEARATE; STEARIC ACID; BUTYLENE GLYCOL

Cremo Medicated Beard Cream

Active Ingredients Purpose

Hydrocortisone 1% Anti-itch

Uses

For temporary relief of itching and minor skin irritation associated to eczema, soaps, detergents, and minor scrapes or scratches

- Keep out of reach of children. If swallowed, get medical help or contact a Poison Control Center right away.

- Stop use and ask a doctor if condition worsens or if symptoms persist for more than 7 days or clear up and occur again within a few days discontinue use and consult a doctor.

Warnings

- For External use only
- When using this product avoid contact with eyes
- If contact occurs, rinse eyes thoroughly with water

Directions

For adults: apply to affected area not more than 3 to 4 times daily.

INACTIVE INGREDIENT

Inactive Ingredients Water, Ethylhexyl Palmitate, Cetyl Alcohol, Glycerin, Butylene Glycol, Glyceryl Stearate, Stearic Acid, Coconut Oil, Cocoa Butter, Caprylyl Glycol, Phenoxyethanol, Hexylene Glycol, Cetearyl Alcohol, Polysorbate 60, Carbomer, Aminomethyl Propanol, Disodium EDTA, Allantoin, Vitamin E Acetate, Aloe Vera Leaf Extract, Organic Tea Tree Leaf Oil, Lavender Oil, Peppermint Oil, Organic Chamomile Blue (German) Flower Oil.

PACKAGE LABEL

Cremo Beard Cream Medicated

Anti-itch formula

2 oz 56g